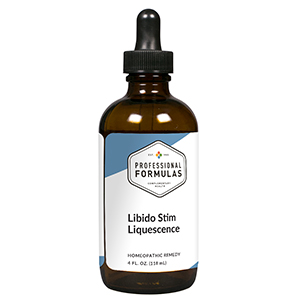 DRUG LABEL: Libido Stim Liquescence
NDC: 63083-3014 | Form: LIQUID
Manufacturer: Professional Complementary Health Formulas
Category: homeopathic | Type: HUMAN OTC DRUG LABEL
Date: 20190815

ACTIVE INGREDIENTS: GLYCERIN 1 [hp_X]/118 mL; PASSIFLORA INCARNATA FLOWERING TOP 1 [hp_X]/118 mL; TURNERA DIFFUSA LEAF 1 [hp_X]/118 mL; VANILLA BEAN 1 [hp_X]/118 mL; 1,2-DISTEAROYL-SN-GLYCERO-3-PHOSPHOCHOLINE 2 [hp_X]/118 mL; BERBERIS VULGARIS ROOT BARK 3 [hp_X]/118 mL; STRYCHNOS IGNATII SEED 3 [hp_X]/118 mL; IODINE 3 [hp_X]/118 mL; SAW PALMETTO 3 [hp_X]/118 mL; YOHIMBINE 3 [hp_X]/118 mL; CHASTE TREE FRUIT 3 [hp_X]/118 mL; PULSATILLA MONTANA WHOLE 4 [hp_X]/118 mL; FERRIC CATION 4 [hp_X]/118 mL; SODIUM CHLORIDE 4 [hp_X]/118 mL; BUFO BUFO CUTANEOUS GLAND 6 [hp_X]/118 mL; SELENIUM 6 [hp_X]/118 mL; ZINC VALERATE DIHYDRATE 6 [hp_X]/118 mL; BOS TAURUS TESTICLE 16 [hp_X]/118 mL; BOS TAURUS OVARY 16 [hp_X]/118 mL
INACTIVE INGREDIENTS: ALCOHOL; WATER

T14

ACTIVE INGREDIENTS

Glycerinum 1X
Passiflora incarnata 1X
Turnera diffusa 1X
Vanilla planifolia 1X
Lecithin 2X
Berberis vulgaris 3X
Ignatia amara 3X
Iodium 3X
Sabal serrulata 3X
Yohimbinum 3X
Agnus castus 3X, 6X
Pulsatilla 4X
Ferrum muriaticum 4X, 6X
Natrum muriaticum 4X, 6X
Bufo rana 6X
Selenium 6X
Zincum valerianicum 6X
Orchic 16X
Ovary 16X

QUESTIONS

Professional Formulas

PO Box 2034 Lake Oswego, OR 97035

INDICATIONS

For the temporary relief of diminished sexual desire or performance, exhaustion, anxiousness, fatigue, or overexertion.*

PURPOSE

*Claims based on traditional homeopathic practice, not accepted medical evidence. Not FDA evaluated.

WARNINGS

In case of overdose, get medical help or contact a poison control center right away.

Keep out of the reach of children.

PREGNANCY OR BREAST FEEDING

If pregnant or breastfeeding, ask a healthcare professional before use.

DIRECTIONS

Place drops under tongue 30 minutes before/after meals. Adults and children 12 years and over: Take one full dropper up to 2 times per day. Consult a physician for use in children under 12 years of age. Not intended for use in infants.

OTHER INFORMATION

Tamper resistant. If seal is broken, do not use. After opening, close container tightly and store at room temperature away from heat.

INACTIVE INGREDIENTS

20% ethanol, purified water.

LABEL

Est 1985

Professional Formulas

Complementary Health

Libido Stim Liquescence

Homeopathic Remedy

4 FL. OZ. (118 mL)